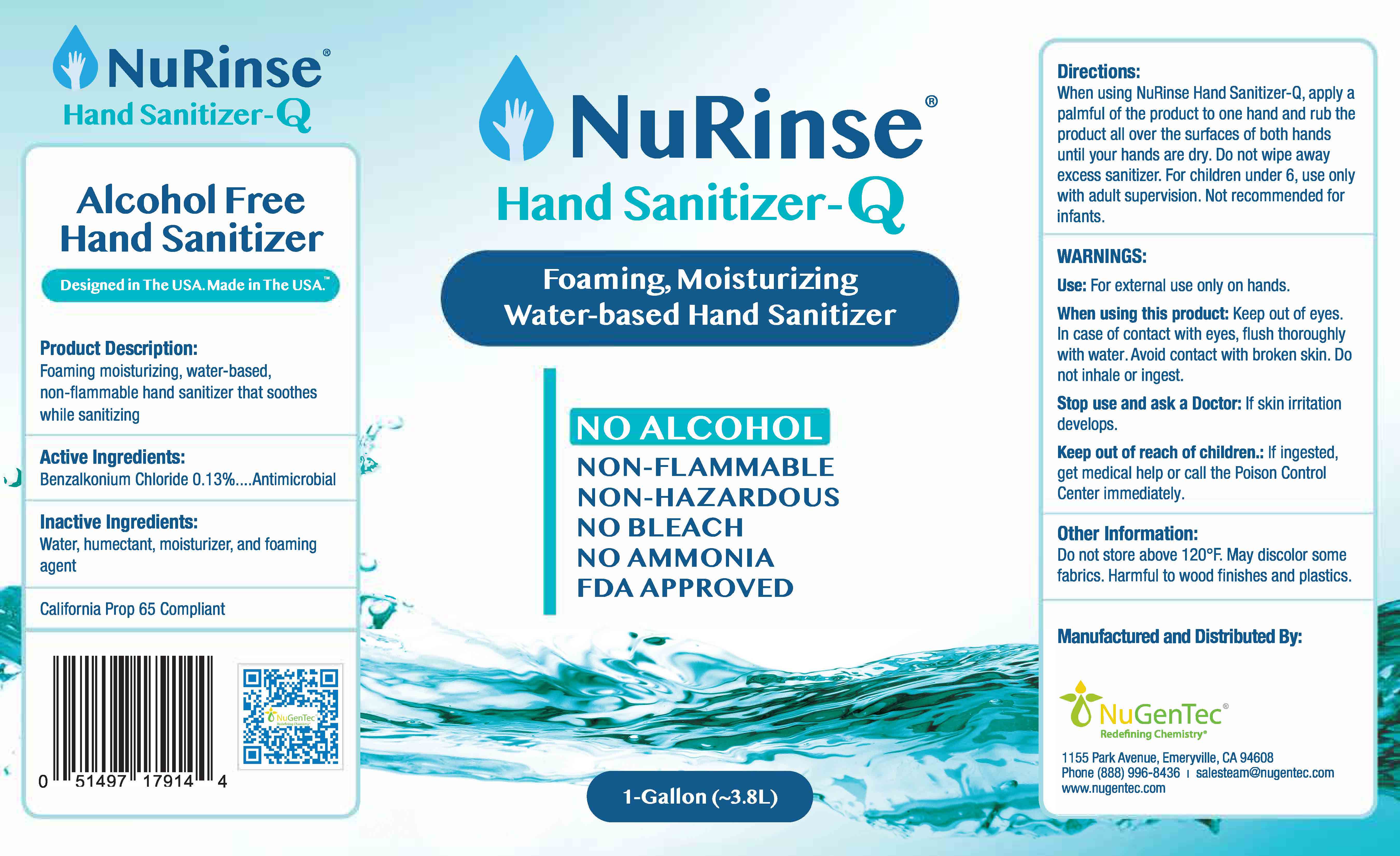 DRUG LABEL: NuRinse Hand Sanitizer-Q
NDC: 77368-903 | Form: LIQUID
Manufacturer: NuGenTec
Category: otc | Type: HUMAN OTC DRUG LABEL
Date: 20221222

ACTIVE INGREDIENTS: BENZALKONIUM CHLORIDE 0.1 mg/100 mL
INACTIVE INGREDIENTS: ANHYDROUS CITRIC ACID 0.08 mg/100 mL; COCAMIDOPROPYL PG-DIMONIUM CHLORIDE PHOSPHATE 0.25 mL/100 mL; WATER; DIHYDROXYETHYL COCAMINE OXIDE 0.25 mL/100 mL; ACETAMIDOETHOXYETHANOL 0.25 mL/100 mL

NuRinse Hand Sanitizer Q

Active Ingredient(s)

Benzalkonium Chloride 0.13%

Purpose

Antiseptic, Hand Sanitizer, Antibacterial

Use

Hand Sanitizer to help reduce bacteria that potentially can cause disease. For use when soap and water are not available.

Warnings

For external use only.

When using this product: Keep out of eyes. In case of contact with eyes, flush thoroughly with water. Avoid contact with broken skin. Do not inhale or ingest.
Stop use and ask a Doctor: If skin irritation develops.
Keep out of reach of children.: If ingested, get medical help or call the Poison Control Center immediately.

Do not use

- in children less than 2 months of age
- on open skin wounds

When using this product keep out of eyes, ears, and mouth. In case of contact with eyes, rinse eyes thoroughly with water.
Stop use and ask a doctor if irritation or rash occurs. These may be signs of a serious condition.
Keep out of reach of children. If swallowed, get medical help or contact a Poison Control Center right away.

Stop use and ask a doctor if irritation or rash occurs. These may be signs of a serious condition.

Keep out of reach of children. If swallowed, get medical help or contact a Poison Control Center right away.

Directions

- When using NuRinse Hand Sanitizer-Q, apply a palmful of the product to one hand and rub the product all over the surfaces of both hands until your hands are dry. Do not wipe away excess sanitizer. For children under 6, use only with adult supervision. Not recommended for infants.

Other information

- Store between 15-30C (59-86F)
- Avoid freezing and excessive heat above 40C (104F)
- Do not store above 120°F.
- May discolor some fabrics.
- Harmful to wood finishes and plastics.

Inactive ingredients

- Purified water USP
- Humectant
- Moisturizer
- Foaming agent

Package Label - Principal Display Panel

750mL is one bottle NDC: 77368-901-75